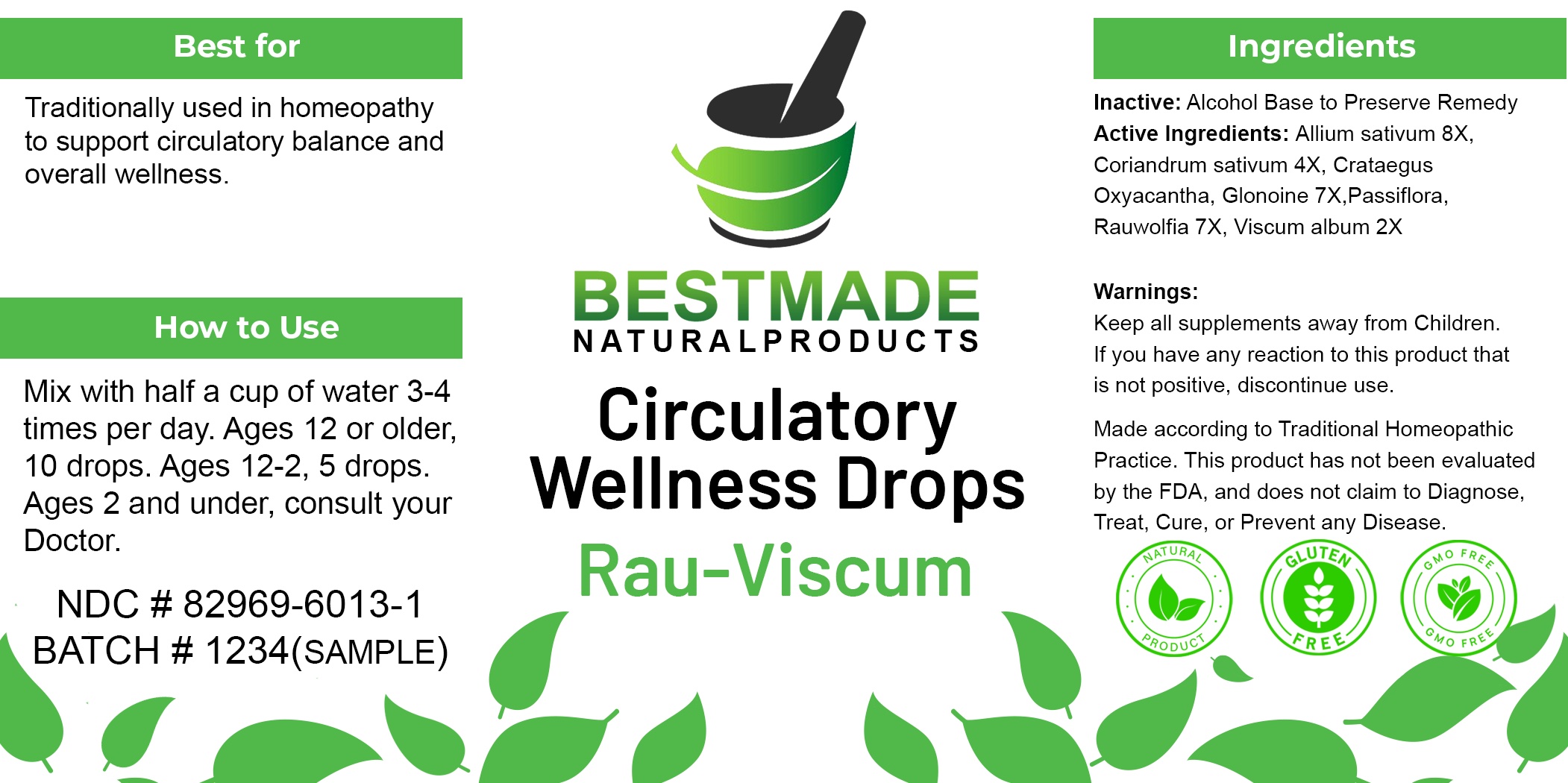 DRUG LABEL: Bestmade Natural Products - Rau-Viscum
NDC: 82969-6013 | Form: LIQUID
Manufacturer: Bestmade Natural Products
Category: homeopathic | Type: HUMAN OTC DRUG LABEL
Date: 20241220

ACTIVE INGREDIENTS: GARLIC 30 [hp_C]/30 [hp_C]; CRATAEGUS OXYACANTHA LEAF 30 [hp_C]/30 [hp_C]; CORIANDER OIL 30 [hp_C]/30 [hp_C]; PASSIFLORA INCARNATA FLOWERING TOP 30 [hp_C]/30 [hp_C]; RAUWOLFIA SERPENTINA 30 [hp_C]/30 [hp_C]; NITROGLYCERIN 30 [hp_C]/30 [hp_C]; VISCUM ALBUM WHOLE 30 [hp_C]/30 [hp_C]
INACTIVE INGREDIENTS: ALCOHOL 30 [hp_C]/30 [hp_C]

Circulatory Wellness Drops - Rau-Viscum

DOSAGE AND ADMINISTRATION

Mix with half a cup of water 3-4 times per day. Ages 12 or older, 10-15 drops. Ages 12-2, 5 drops. Ages 2 and under, consult your Doctor.

INDICATIONS AND USAGE

Traditionally used in homeopathy to support circulatory balance and overall wellness.

Inactive: Alcohol Base to Preserve Remedy

ACTIVE INGREDIENT

Allium sativum 8X: 0.20ml

Coriandrum sativum 4X: 0.30ml

Crataegus oxyacantha Ø: 0.70ml

Glonoine 7X: 0.30ml

Passiflora Ø: 0.80ml

Rauwolfia 7X: 1.20ml

Viscum album 2X: 1.50ml

Keep all supplements away from Children.

PURPOSE

Traditionally used in homeopathy to support circulatory balance and overall wellness.

Warnings:
Keep all supplements away from Children.
If you have any reaction to this product that
is not positive, discontinue use.

Entire package label